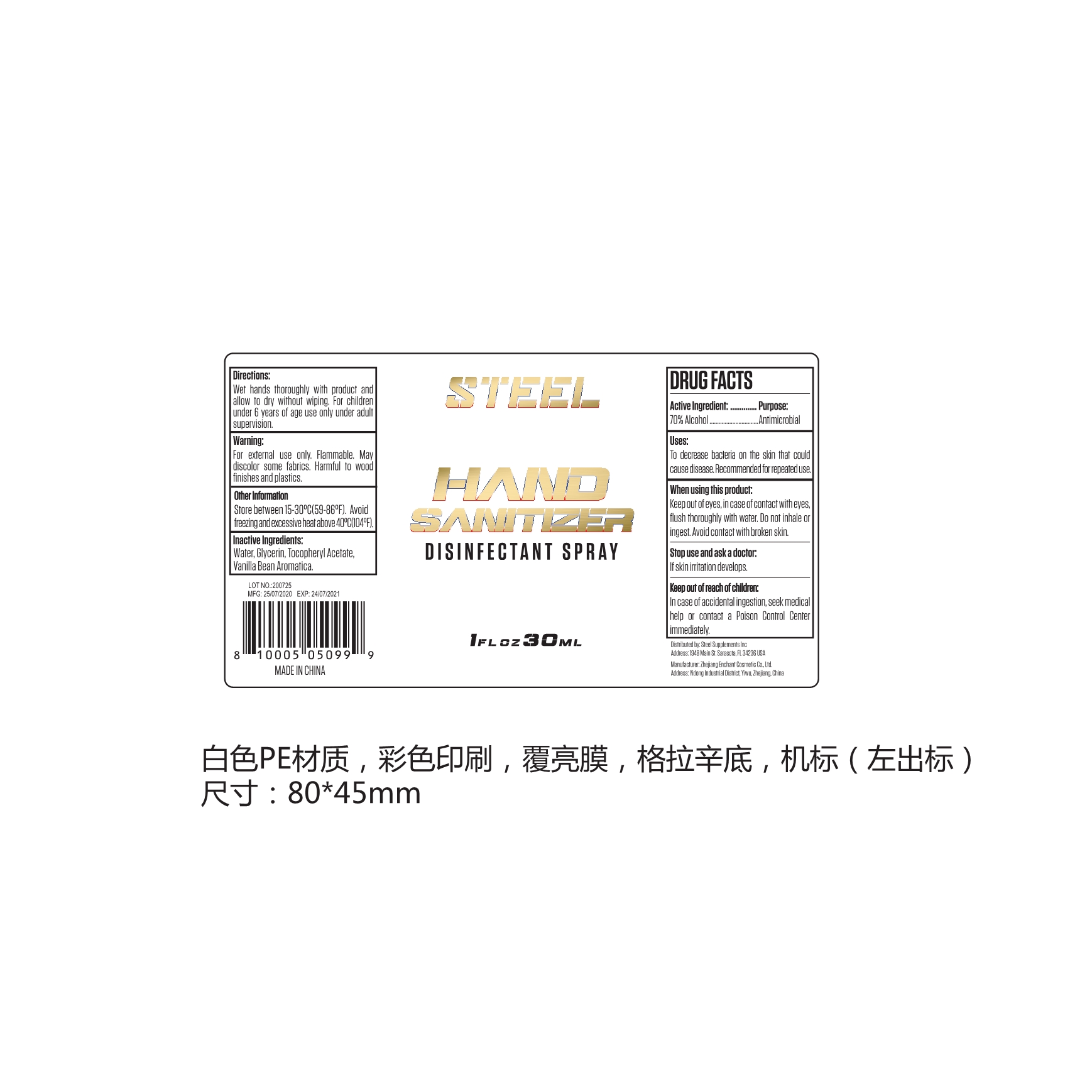 DRUG LABEL: HAND SANITIZER
NDC: 79931-001 | Form: SPRAY
Manufacturer: Steel Supplements, Inc.
Category: otc | Type: HUMAN OTC DRUG LABEL
Date: 20220105

ACTIVE INGREDIENTS: ALCOHOL 70 mL/100 mL
INACTIVE INGREDIENTS: VANILLA BEAN; GLYCERIN; TOCOPHEROL; WATER

Steel Supplements, Inc.
30mL HAND SANITIZER 79931-001-01

Active Ingredient(s)

70% Alcohol

Purpose

Antimicrobial

Use

To decrease bacteria on the skin that could cause disease. Recommended for repeated use.

Warnings

- For external use only.
- Flammable.
- May discolor some fabrics.
- Harmful to wood finishes and plastics.

WHEN USING

Keep out of eyes, in case of contact with eyes, flush thoroughly with water. Do not inhale or ingest. Avoid contact with broken skin.

Stop use and ask a doctor if skin irritation develops.

Keep out of reach of children. In case of accidental ingestion, seek medical help or contact a Poison Control Center immediately.

Directions

- Wet hands thoroughly with product and allow to dry without wiping.
- For children under 6 years of age only under adult supervision.

Other information

- Store between 15-30℃(59-86℉).
- Avoid freezing and excessive heat above 40℃(104℉).

Inactive ingredients

Water, Glycerin, Tocopheryl Acetate, Vanilla Bean Aromatica.

Package Label - Principal Display Panel

30 mL in 1 BOTTLE, NDC: 79931-001-01